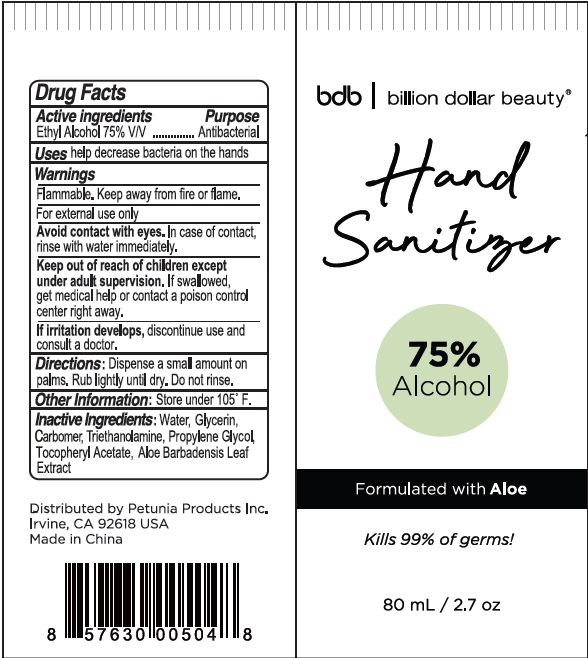 DRUG LABEL: Billion Dollar Beauty Hand Sanitizer Formulated with Aloe
NDC: 74149-014 | Form: GEL
Manufacturer: Yiwu Yangjie Daily Chemicals Co.,Ltd.
Category: otc | Type: HUMAN OTC DRUG LABEL
Date: 20200514

ACTIVE INGREDIENTS: alcohol 75 mL/100 mL
INACTIVE INGREDIENTS: WATER; PROPYLENE GLYCOL; ALOE VERA LEAF; CARBOMER 934; GLYCERIN; .ALPHA.-TOCOPHEROL ACETATE; TROLAMINE

Drug facts

Active ingredient Purpose

Ethyl Alcohol 75% V/V ... Antibacterial

PURPOSE

- help decrease bacteria on the hands

KEEP OUT OF REACH OF CHILDREN

Children must be under adult supervision. If swallowed, get medical help or contact a poison control center right away.

Except of under adult supervision.

Directions:

Dispense a small amount on palms. Rub lightly until dry. Do not rinse.

WARNINGS

For external use only.
Flammable. Keep away from fire or flame.

Avoid contact with eyes. In case of contact, rinse with water immediately.

If irritation develops, discontinue use and consult a doctor.

OTHER INFORMATION:

Store under 105℉

DOSAGE AND ADMINISTRATION

Dispense a small amount on palms, rub lightly until dry. Do not rinse.

INACTIVE INGREDIENT

Water, Glycerin, Carbomer, Triethanolamine, Propylene Glycol, Tocopheryl Acetate, Aloe Barbadensis Leaf Extract